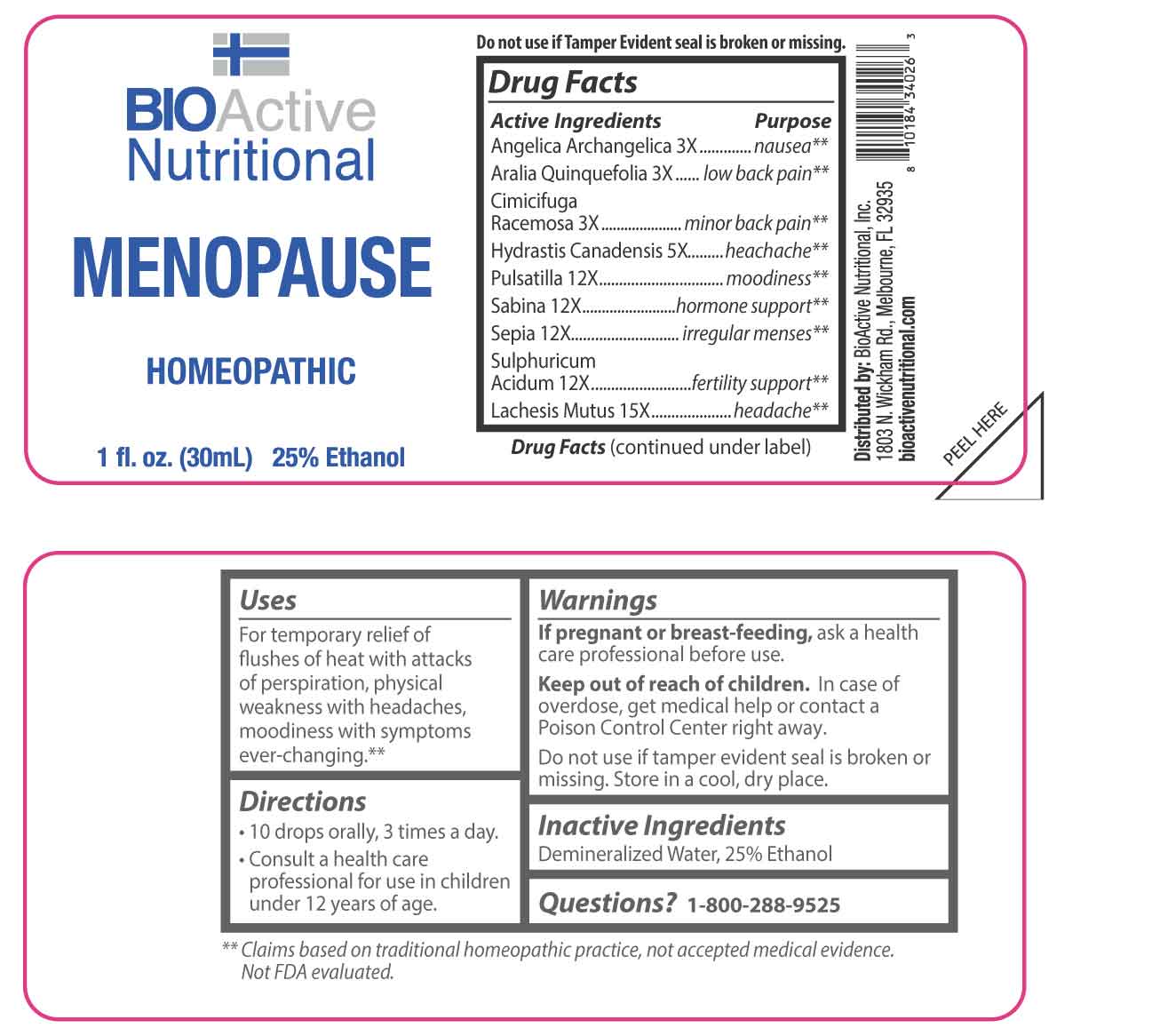 DRUG LABEL: Menopause
NDC: 43857-0446 | Form: LIQUID
Manufacturer: BioActive Nutritional, Inc.
Category: homeopathic | Type: HUMAN OTC DRUG LABEL
Date: 20250624

ACTIVE INGREDIENTS: ANGELICA ARCHANGELICA ROOT 3 [hp_X]/1 mL; AMERICAN GINSENG 3 [hp_X]/1 mL; BLACK COHOSH 3 [hp_X]/1 mL; GOLDENSEAL 5 [hp_X]/1 mL; PULSATILLA VULGARIS WHOLE 12 [hp_X]/1 mL; JUNIPERUS SABINA LEAFY TWIG 12 [hp_X]/1 mL; SEPIA OFFICINALIS JUICE 12 [hp_X]/1 mL; SULFURIC ACID 12 [hp_X]/1 mL; LACHESIS MUTA VENOM 15 [hp_X]/1 mL
INACTIVE INGREDIENTS: WATER; ALCOHOL

DRUG FACTS:

ACTIVE INGREDIENTS:

Angelica Archangelica 3X, Aralia Quinquefolia 3X, Cimicifuga Racemosa 3X, Hydrastis Canadensis 3X, Pulsatilla 12X, Sabina 12X, Sepia 12X, Sulphuricum Acidum 12X, Lachesis Mutus 15X.

PURPOSE:

Angelica Archangelica - nausea,** Aralia Quinquefolia – low back pain,** Cimicifuga Racemosa – minor back pain,** Hydrastis Canadensis - headache,** Pulsatilla - moodiness,** Sabina – hormone support,** Sepia – irregular menses,** Sulphuricum Acidum – fertility support,** Lachesis Mutus – headache**

**Claims based on traditional homeopathic practice, not accepted medical evidencel. Not FDA evaluated.

USES:

For temporary relief of flushes of heat with attacks of perspiration, physical weakness with headaches, moodiness with symptoms ever-changing.

**Claims based on traditional homeopathic practice, not accepted medical evidencel. Not FDA evaluated.

WARNINGS:

If pregnant or breast-feeding, ask a health care professional before use.

Keep out of reach of children. In case of overdose, get medical help or contact a Poison Control Center right away.

Do not use if tamper evident seal is broken or missing.

Store in a cool, dry place.

KEEP OUT OF REACH OF CHILDREN:

In case of overdose, get medical help or contact a Poison Control Center right away.

DIRECTIONS:

• 10 drops orally, 3 times a day.

• Consult a health care professional for use in children under 12 years of age.

INACTIVE INGREDIENTS:

Demineralized Water, 25% Ethanol

QUESTIONS:

Distributed by:

BioActive Nutritional, Inc.

1803 N. Wickham Rd.

Melbourne, FL 32935

bioactivenutritional.com

1-800-288-9525

PACKAGE LABEL DISPLAY:

BIOActive Nutritional

MENOPAUSE

HOMEOPATHIC

1 fl. oz. (30mL)